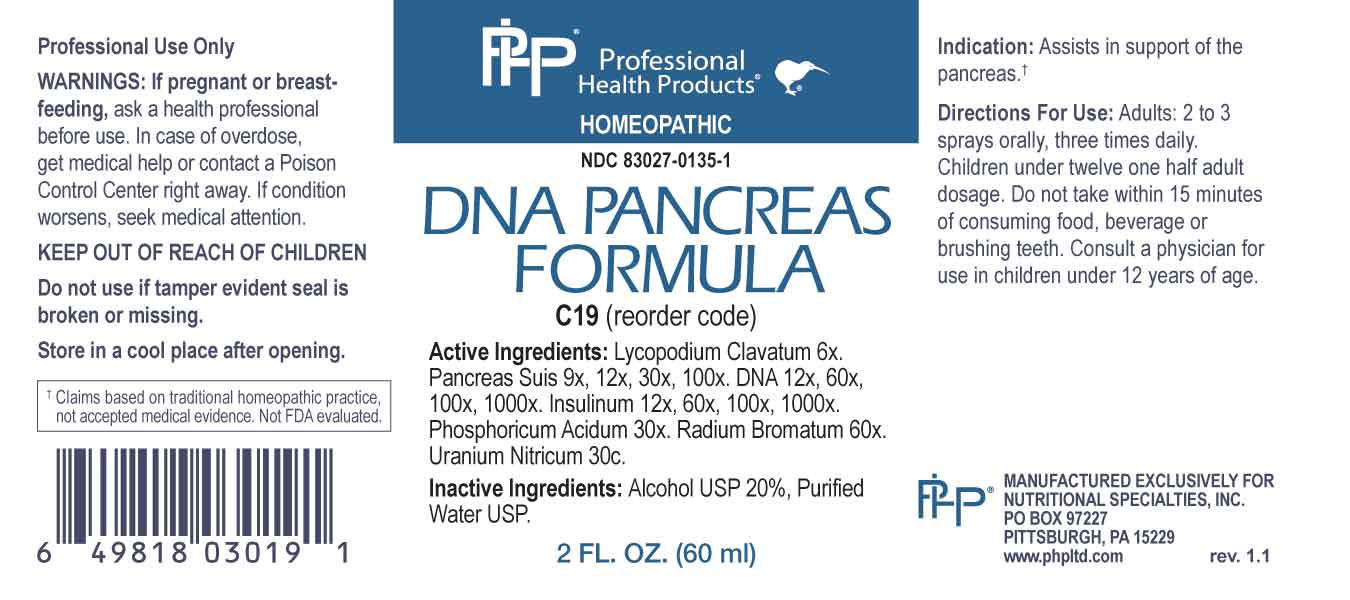 DRUG LABEL: DNA Pancreas Formula
NDC: 83027-0135 | Form: SPRAY
Manufacturer: Nutritional Specialties, Inc.
Category: homeopathic | Type: HUMAN OTC DRUG LABEL
Date: 20240529

ACTIVE INGREDIENTS: LYCOPODIUM CLAVATUM SPORE 6 [hp_X]/1 mL; SUS SCROFA PANCREAS 9 [hp_X]/1 mL; HERRING SPERM DNA 12 [hp_X]/1 mL; INSULIN HUMAN 12 [hp_X]/1 mL; PHOSPHORIC ACID 30 [hp_X]/1 mL; RADIUM BROMIDE 60 [hp_X]/1 mL; URANYL NITRATE HEXAHYDRATE 30 [hp_C]/1 mL
INACTIVE INGREDIENTS: WATER; ALCOHOL

DRUG FACTS:

ACTIVE INGREDIENTS:

Lycopodium Clavatum 6X, Pancreas Suis 9X, 12X, 30X, 100X, DNA 12X, 60X, 100X, 1000X, Insulinum 12X, 60X, 100X, 1000X, Phosphoricum Acidum 30X, Radium Bromatum 60X, Uranium Nitricum 30C.

PURPOSE:

Assists in support of the pancreas.†

†Claims based on traditional homeopathic practice, not accepted medical evidence. Not FDA evaluated.

WARNINGS:

Professional Use Only

If pregnant or breast-feeding, ask a health professional before use.

In case of overdose, get medical help or contact a Poison Control Center right away.

If condition worsens, seek medical attention.

KEEP OUT OF REACH OF CHILDREN

Do not use if tamper evident seal is broken or missing.

Store in a cool place after opening

KEEP OUT OF REACH OF CHILDREN:

In case of overdose, get medical help or contact a Poison Control Center right away.

DIRECTIONS:

Adults: 2 to 3 sprays orally, three times daily. Children under twelve one half adult dosage. Do not take within 15 minutes of consuming food, beverage or brushing teeth. Consult a physician for use in children under 12 years of age.

INDICATIONS:

Assists in support of the pancreas.†

†Claims based on traditional homeopathic practice, not accepted medical evidence. Not FDA evaluated.

INACTIVE INGREDIENTS:

Alcohol USP 20%, Purified Water USP.

QUESTIONS:

MANUFACTURED EXCLUSIVELY FOR

NUTRITIONAL SPECIALTIES, INC.

PO BOX 97227

PITTSBURG, PA 15229

www.phpltd.com

PACKAGE LABEL DISPLAY:

Professional

Health Products

HOMEOPATHIC

NDC 83027-0135-1

DNA PANCREAS

FORMULA

2 FL. OZ (60 ml)